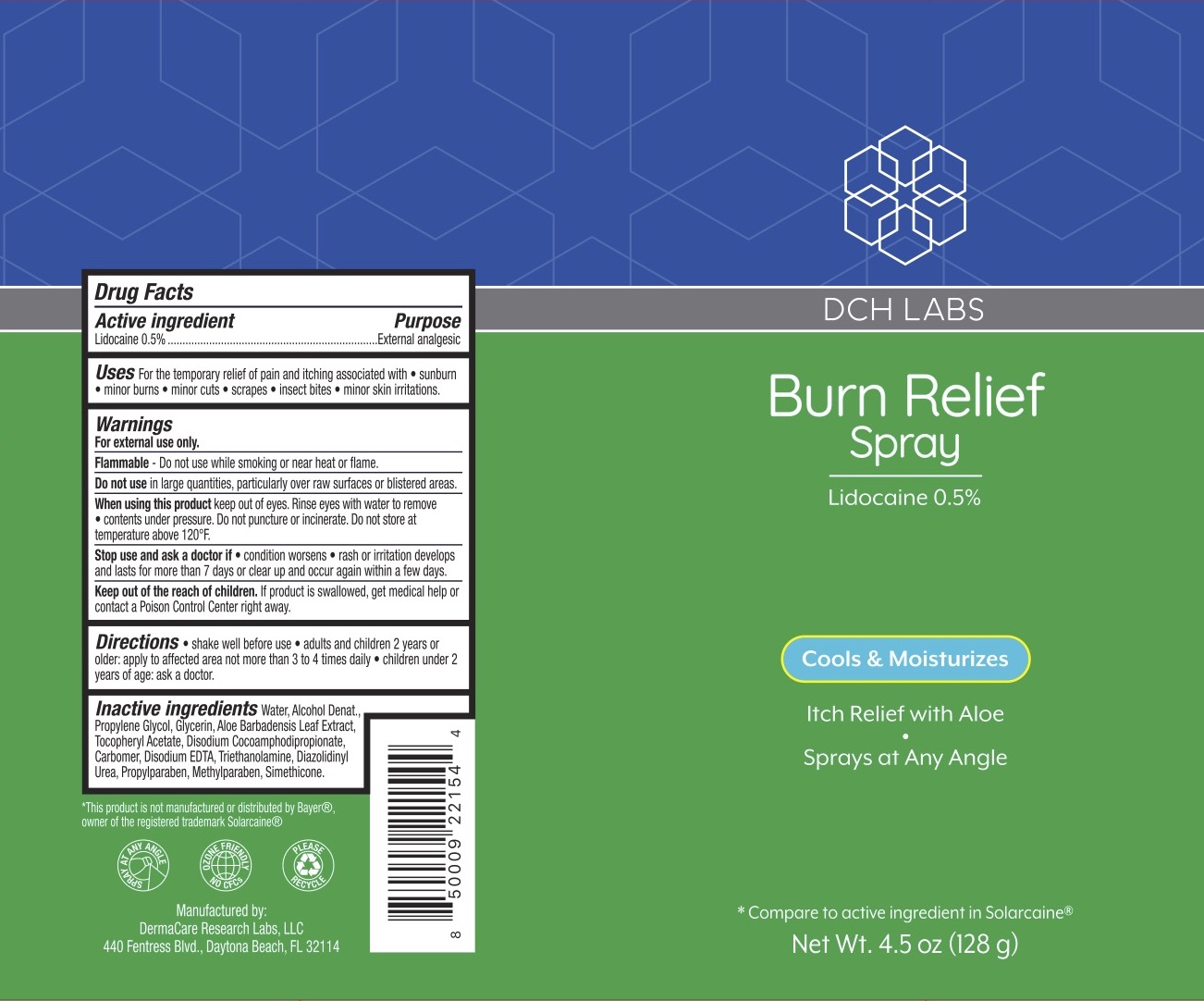 DRUG LABEL: DCH Burn Relief
NDC: 72839-021 | Form: SPRAY
Manufacturer: Derma Care Research Labs
Category: otc | Type: HUMAN OTC DRUG LABEL
Date: 20241219

ACTIVE INGREDIENTS: LIDOCAINE 0.5 g/100 g
INACTIVE INGREDIENTS: WATER; GLYCERIN; ALCOHOL; PROPYLENE GLYCOL; EDETATE DISODIUM; TROLAMINE; ALOE VERA LEAF; CARBOMER 940; POLYSORBATE 80; DIAZOLIDINYL UREA; PROPYLPARABEN; DISODIUM COCOAMPHODIPROPIONATE; METHYLPARABEN; SILICON DIOXIDE

DCH Burn Relief Spray, Lidocaine 0.5%

ACTIVE INGREDIENT

Lidocaine HCl 0.5%

PURPOSE

External Analgesic.

DOSAGE AND ADMINISTRATION

For the temporary relief of pain and itching due to sunburn, minor burns, insect bites, minor cuts, scrapes, and minor skin irritations.

WARNINGS

For external use only.

Flammable--do not use while smoking or near heat or flame. Do not use in large quantities, particularly over raw surfaces or blistered areas.

When using this product avoid contact with eyes. Rinse with water to remove. Contents under pressure. Do not puncture or incinerate. Do not store at temperature above 120F.

Stop use and ask a doctor if the condition worsens or symptoms persist for more than 7 days or clear up and occur again within a few days.

Keep out of reach of children. If the product is swallowed, get medical help or contact a Poison Control Center right away.

INDICATIONS AND USAGE

Shake well before use. Adults and children 2 years and older: apply to the affected area, not more than 3 to 4 times a day. Children under 2 years of age: ask a doctor. To apply to face, spray in palm of hand and gently apply.

INACTIVE INGREDIENT

Water, Alcohol Denat., Propylene Glycol, Glycerin, Aloe Barbadensis Leaf Extract, Tocopheryl Acetate, Disodium Cocoamphodipipropionate, Carbomer, Disodium EDTA, Triethanolamine, Diazolidinyl Urea, Propylparaben, methylparaben, Simethicone.